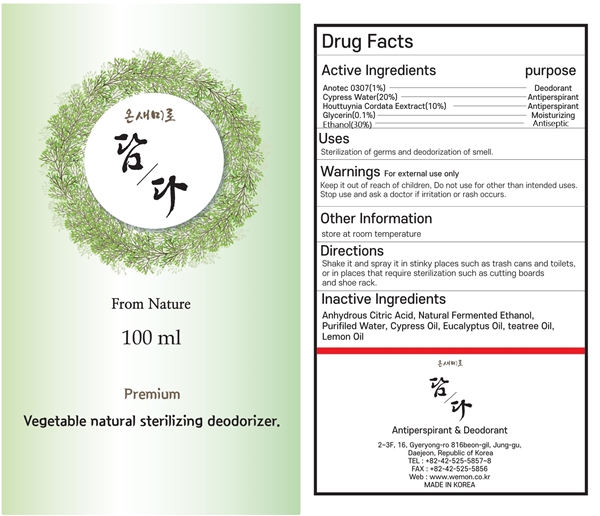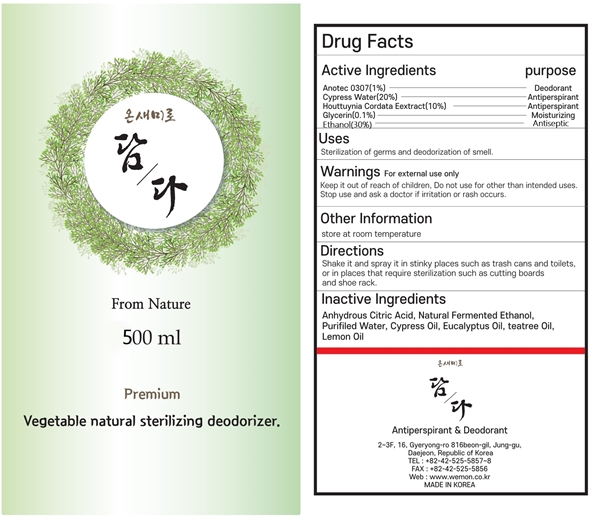 DRUG LABEL: Onsaemiro Damda
NDC: 82341-302 | Form: LIQUID
Manufacturer: WEMON
Category: otc | Type: HUMAN OTC DRUG LABEL
Date: 20231219

ACTIVE INGREDIENTS: HOUTTUYNIA CORDATA FLOWERING TOP 5 g/100 mL; GLYCERIN 0.1 g/100 mL; EUCALYPTUS OIL 0.3 g/100 mL; CHAMAECYPARIS OBTUSA WHOLE 25 g/100 mL; WHITE PINE OIL 0.3 g/100 mL; OLIVE OIL 0.3 g/100 mL; SORBITOL 0.3 g/100 mL; ALCOHOL 30 mL/100 mL
INACTIVE INGREDIENTS: WATER; ANHYDROUS CITRIC ACID; TEA TREE OIL; LEMON OIL

Active Ingredients

WHITE PINE OIL
ALCOHOL
SORBITOL
EUCALYPTUS OIL
HOUTTUYNIA CORDATA FLOWERING TOP
GLYCERIN PDC6A3C0OX
CHAMAECYPARIS OBTUSA WHOLE
OLIVE OIL

purpose

Deodorant
Antiperspirant
anticeptic

Uses

Sterilization of germs and deodorization of smell.

Warnings

Do not use for other than intended uses.

Warnings

Stop use and ask a doctor if irritation or rash occurs.

Directions

Shake it and spray it in stinky places such as trash cans and toilets,
or in places that require sterilization such as cutting boards

Warnings

Keep it out of reach of children, Do not use for other than intended uses.

Inactive Ingredients

LEMON OIL, TEA TREE OIL, Cypress Oil, WATER

other info

store at room temperature

warnings

For external use only

label

82341-302-01

82341-302-02